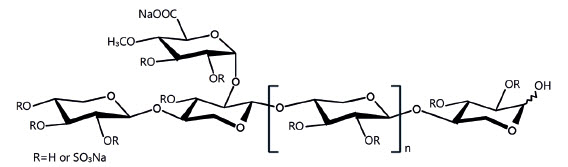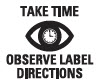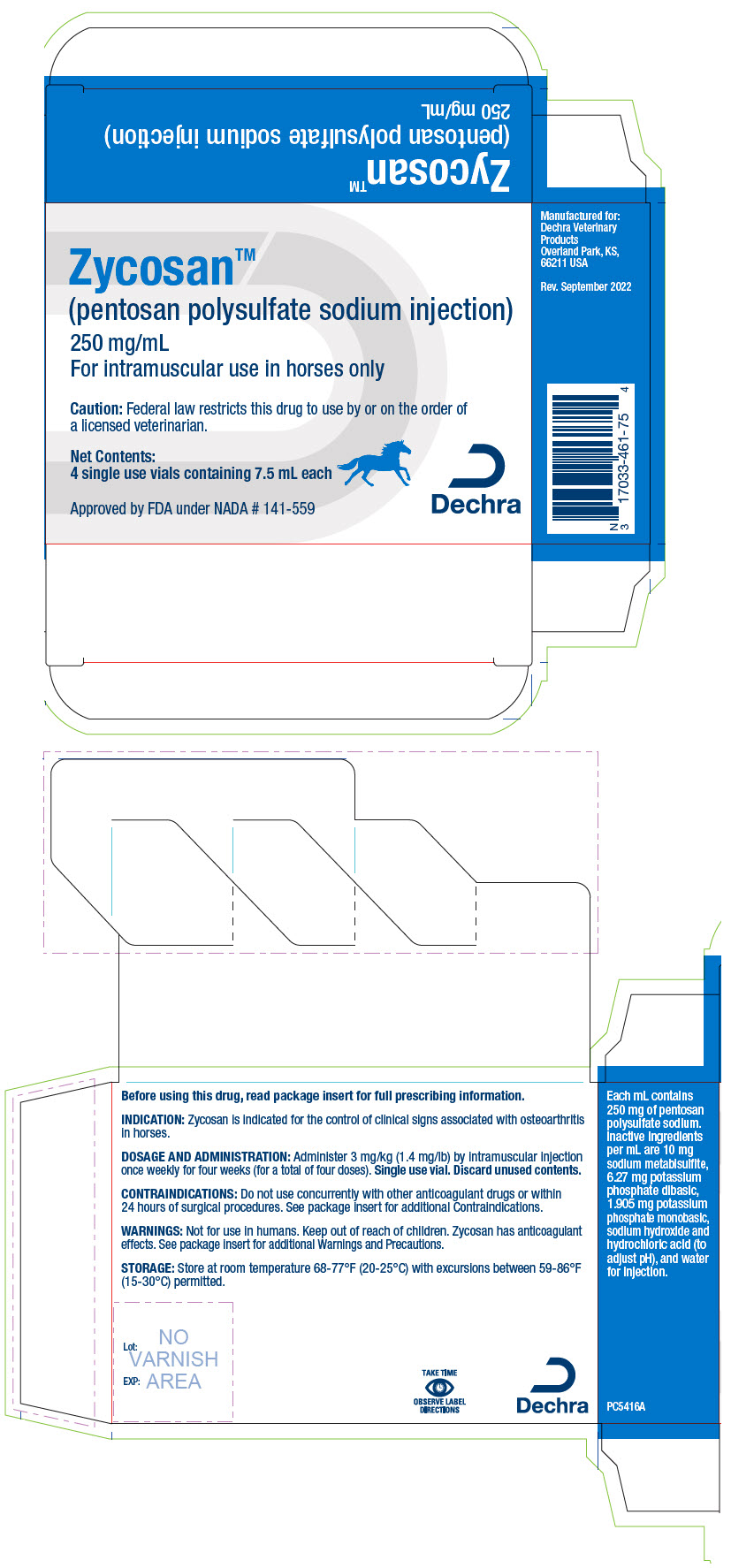 DRUG LABEL: Zycosan
NDC: 17033-461 | Form: INJECTION, SOLUTION
Manufacturer: Dechra Veterinary Products
Category: animal | Type: PRESCRIPTION ANIMAL DRUG LABEL
Date: 20241202

ACTIVE INGREDIENTS: PENTOSAN POLYSULFATE SODIUM 250 mg/1 mL

Zycosan®
(pentosan polysulfate sodium injection)

250 mg/mL

For intramuscular use in horses only

CAUTION:

Federal law restricts this drug to use by or on the order of a licensed veterinarian.

DESCRIPTION:

Zycosan contains pentosan polysulfate sodium, a semi-synthetic polysulfated xylan. It is a pale yellow to brownish yellow, clear, sterile solution. Each milliliter of Zycosan contains 250 mg of pentosan polysulfate sodium. Inactive ingredients per mL are 10 mg sodium metabisulfite, 6.27 mg potassium phosphate dibasic, 1.905 mg potassium phosphate monobasic, sodium hydroxide and hydrochloric acid (to adjust pH), and water for injection. The molecular weight of pentosan polysulfate sodium is 4000 - 7500 Daltons.

The structural formula is:

INDICATION:

For the control of clinical signs associated with osteoarthritis in horses.

DOSAGE AND ADMINISTRATION:

Administer 3 mg/kg (1.4 mg/lb) by intramuscular injection once weekly for four weeks (for a total of four doses). Zycosan is provided in a single use vial and does not contain a preservative. Discard unused vial contents.

CONTRAINDICATIONS:

Horses with hypersensitivity to pentosan polysulfate sodium or any of the inactive ingredients in Zycosan should not receive Zycosan. Do not use Zycosan concurrently with other anticoagulant drugs. Do not use in horses with clotting disorders or within 24 hours of surgical procedures (see Warnings and Precautions).

WARNINGS AND PRECAUTIONS:

User Safety Warnings:

Not for use in humans. Keep out of reach of children. Pentosan polysulfate sodium is a weak anticoagulant. Caution should be used when administering Zycosan if you are taking an anticoagulant. In case of accidental self-injection, seek immediate medical attention. If product comes into contact with skin, rinse skin thoroughly with water and seek medical attention if needed. To obtain a Safety Data Sheet (SDS), contact Dechra at (866) 933-2472.

Animal Safety Warnings and Precautions:

Zycosan has been shown to prolong coagulation parameters up to 24 hours after injection, therefore caution should be used when administering this drug before or after strenuous activities (see Target Animal Safety). Due to the anticoagulant effects, this drug may exacerbate Exercise Induced Pulmonary Hemorrhage (EIPH).

The concurrent use of NSAIDs with Zycosan has not been evaluated. Due to the anticoagulant effects of Zycosan and known anticoagulant effects of some NSAIDs, caution should be used if NSAIDs are concurrently administered. Horses concurrently treated with Zycosan and NSAIDs should be monitored for hemorrhage or other clinical signs of abnormal bleeding (e.g., petechiae, ecchymosis, or epistaxis).

The safety of long-term repeat use of Zycosan has not been evaluated.

Pigmentary changes in the retina (pigmentary maculopathy) have been reported in human patients following long-term oral use of pentosan polysulfate sodium. It is not known if a similar finding occurs in horses.

The safe use of Zycosan has not been evaluated in breeding, pregnant, or lactating horses.

Other Warnings:

Do not use in horses intended for human consumption.

ADVERSE REACTIONS:

In a clinical field effectiveness study, two hundred thirty-seven horses (120 Zycosan and 117 saline control) were evaluated for field safety (see Effectiveness). All doses of Zycosan were administered in the neck muscle.

Injection site reactions were the most frequently reported adverse reactions during the study. Injection site reactions were associated with clinicopathology changes in some cases. Other adverse reactions reported in more than one horse were prolongation of coagulation parameters (activated partial thromboplastin time (aPTT) and prothrombin time (PT)), lethargy, behavior changes, and colic. Adverse reactions are summarized in Table 1. Horses may have experienced more than one of the observed adverse reactions.

Table 1: Adverse Reactions
Adverse Reaction | Number (%) of Zycosan™ treated horses (N=120) | Number (%) of Saline treated horses (N=117)
Immediate or Peri-Dosing Injection Site Reaction [Occurring 0-3 hours post-injection; clinical signs included pain, heat, swelling, edema, redness, or neck muscle cramping. Horses may have experienced more than one episode.] | 21 (18%) | 4 (3%)
Delayed Injection Site Reaction [Occurring more than 3 hours post-injection; observations included pain, heat, swelling, edema, redness, or neck muscle cramping. Pain was exhibited local to the injection site and as reluctance to eat, drink, or move the neck or head. Horses may have experienced more than one episode.] | 13 (11%) | 3 (3%)
Prolonged aPTT (post-treatment) | 18 (15%) | 1 (1%)
Prolonged PT (post-treatment) | 5 (4%) | 1 (1%)
Lethargy | 14 (12%) | 7 (6%)
Behavior Change [Observations included aggression, stomping, pawing, agitation, anxiousness, overactivity, quietness and/or depression, or unsettledness.] | 10 (8%) | 8 (7%)
Colic | 2 (2%) | 0 (0%)
Elevated Sorbitol Dehydrogenase (SDH) | 1 (1%) | 0 (0%)
Stiffness | 1 (1%) | 0 (0%)

Injection site reactions (heat, pain, swelling/edema, or redness) occurred more frequently and were generally more severe in Zycosan treated horses as compared to control horses over the course of the study. Several Zycosan treated horses had injection site reactions following more than one injection. The onset of reactions ranged from 0 hours to 3 days post injection. The duration of the reactions ranged from 1 to 5 days. Most reactions resolved without treatment.

Injection site reactions in Zycosan treated horses were predominantly characterized by swelling/edema ranging in size from 0.2 cm to 15 cm at their widest point. Pain was the most commonly observed concurrent clinical sign associated with the swelling/edema in Zycosan treated horses. Pain was generally exhibited local to the injection site and as reluctance to eat, drink, or move the neck or head. Lethargy or depression were reported concurrently in some horses. One Zycosan treated horse had neck muscle cramping observed concurrently.

One Zycosan treated horse experienced swelling accompanied by heat and pain at the injection site along with mild hyperglycemia, an increase in its white blood cell count and neutrophilia. This horse recovered without treatment.

Two Zycosan treated horses developed large (15 cm) swellings along with pain and heat at the injection site beginning 1 to 2 days following injection. Both horses concurrently showed mild hyperbilirubinemia, mild hyperglycemia, mild neutrophilia, and mild monocytosis on clinical pathology. One of these horses was reluctant to move its head or neck and was noted to be tachypneic the day following injection. The second horse showed concurrent clinical signs of anorexia, depression, and fever. Both horses were removed from the study and treated with flunixin meglumine. The horse with concurrent fever was also treated with an oral antibiotic for 5 days. Both horses recovered within 5 days from the onset of clinical signs.

Coagulation parameters were evaluated pre-treatment and 3 hours post-treatment following the first (study day 0), third (study day 14) and fourth (study day 21) injection. Mean post-treatment values for aPTT in the Zycosan treated group increased by approximately 19 seconds at each study timepoint but remained within the laboratory reference range.

Clinically relevant prolongation of aPTT values occurred post-treatment in 18 Zycosan treated horses, with some horses experiencing prolongation of aPTT at multiple timepoints. Clinically relevant prolongation in PT occurred post-treatment in 5 Zycosan treated horses. Three Zycosan treated horses showed concurrent clinically relevant prolongation in aPTT and PT at study day 0 (N=1) or study day 14 (N=2). One of the horses with post-treatment prolongation of aPTT and PT at study day 14 was concurrently reported to have an injection site reaction. Clinical signs of bleeding or thrombocytopenia were not observed in any horses with prolongation of coagulation parameters.

Two Zycosan treated horses developed clinical signs of colic (lethargy, generalized discomfort, decreased appetite, decreased water intake, and/or decreased manure output) within 12 hours following treatment after the third injection. One horse was diagnosed with a pelvic flexure impaction. One horse was noted to display a markedly lowered head position prior to colic signs and was removed from the study. In both cases, colic signs resolved within 24 hours with symptomatic treatment.

One Zycosan treated horse showed an increase in SDH in conjunction with trending increases in aspartate aminotransferase (AST) and alanine transaminase (ALT) that did not exceed the reference range. Concurrent clinically relevant changes in γ-glutamyl transferase (GGT) or clinical signs were not observed in this horse.

CONTACT INFORMATION:

Contact Dechra at (866) 933-2472 or www.dechra-us.com for technical assistance, or to obtain a copy of the Safety Data Sheet (SDS). To report suspected adverse drug experiences, contact Dechra at (866) 933-2472.

For additional information about adverse drug experience reporting for animal drugs, contact FDA at 1-888-FDA-VETS, or online at http://www.fda.gov/reportanimalae.

CLINICAL PHARMACOLOGY:

Pentosan polysulfate sodium is a low molecular weight heparin-like compound. It is chemically and structurally similar to heparin and other glycosaminoglycans (GAG). Pentosan polysulfate sodium has anticoagulant and fibrinolytic effects. The mechanism of action for pentosan polysulfate sodium is unknown but is thought to include stimulation of hyaluronic acid and GAG synthesis in damaged joints, inhibition of proteolytic enzymes (including metalloproteinases), and scavenging of free radicals. Pentosan polysulfate sodium may also modulate receptor-mediated binding of cytokines.

EFFECTIVENESS:

Two hundred and thirty-seven (237) client-owned horses with osteoarthritis (82 non-pregnant/non-lactating mares, 151 geldings, and 4 stallions), aged 3-32 years old, of various breeds, and weighing between 153-904 kg (337 to 1989 pounds) were enrolled in a controlled, randomized, masked, multi-site field study. One hundred and twenty (120) horses received Zycosan administered at 3 mg/kg (1.4 mg/lb) via intramuscular injection and 117 horses received a volume matched negative (saline) control. All intramuscular injections were administered in the neck once weekly for four weeks. Two hundred and twenty-two (222) horses (109 Zycosan and 113 saline control) were included in the evaluation of effectiveness (final effectiveness analysis).

Enrolled horses had a unilateral lameness between Grade 2 and 4 (≥2 and ≤4) on the American Association of Equine Practitioners (AAEP) Lameness Scale [AAEP lameness grades are defined as follows: 0: Lameness not perceptible under any circumstances; 1: Lameness is difficult to observe and is not consistently apparent, regardless of circumstances (e.g., under saddle, circling, inclines, hard surface, etc.); 2: Lameness is difficult to observe at a walk or when trotting in a straight line but consistently apparent under certain circumstances (e.g. weight-carrying, circling, inclines, hard surface, etc.); 3: Lameness is consistently observable at a trot under all circumstances; 4: Lameness is obvious at a walk; 5: Lameness produces minimal weight bearing in motion and/or at rest or a complete inability to move.] and a diagnosis of osteoarthritis based on a lameness examination and radiographs. Nerve blocks were permitted to confirm and localize the clinical lameness.

Horses with prior diagnosis of bleeding issues (including exercise induced pulmonary hemorrhage (EIPH)), or those where trauma or bleeding were expected to occur during the study time-period (e.g., from planned surgery) were not enrolled. Horses receiving systemic non-steroidal anti-inflammatory drugs at the start of the study were not enrolled.

Horses were assigned a baseline AAEP lameness grade at enrollment (study day 0) and were evaluated for lameness at study days 7, 14, 21, and 28. Horses were considered a treatment success if the baseline lameness grade in the identified limb improved by ≥ 1 AAEP lameness grade on Day 28.

Table 2 summarizes the treatment success rate in each treatment group. The treatment success rate was 57% for horses in the Zycosan group and 36% in the saline control group.

Table 2: Day 28 Treatment Success Rates
Treatment Group | Number of Horses | Percent Success
Zycosan | 109 | 57.00%
Negative Control (saline) | 113 | 36.26%

The difference in the success rates between the two treatments was not statistically significant (p=0.0548). However, the point estimates of the treatment success rate appeared to indicate a clinically relevant effect size. Sensitivity analyses showed that due to variability across sites, the results varied depending on the inclusion of a small number of cases (n=3). The persuasive size of the effect in the larger proportion of the study supports the conclusion that this field study demonstrated substantial evidence of effectiveness.

TARGET ANIMAL SAFETY:

In a laboratory margin of safety study, Zycosan or saline control was administered to 32 healthy adult horses aged 2 to 7 years, in the neck muscle at 3 mg/kg (1× maximum exposure dose, 8 horses), 9 mg/kg (3×, 8 horses), and 15 mg/kg (5×, 8 horses) once weekly for 12 weeks. Eight horses in a control group were administered saline at a volume equivalent to the dosing of the 5× horses.

Pain and swelling at the injection site were noted in all Zycosan treated horses at various study timepoints. At study day 21 (after 4 doses), all 5× horses (8/8) had injection site reactions and 5/8 of the 1× horses and 5/8 of the 3× horses had injection site reactions consisting of pain and swelling.

In three horses receiving a 5× dose, the pain on injection was associated with muscle spasms and stiffness, holding head low, lethargy, and decreased feed intake. The average injection site reaction lasted between 2-6 days in the 5× group; 0-4 days in the 3× group; and 0-2 days in the 1× group. One 3× horse required treatment with flunixin meglumine and oral electrolytes due to pain and swelling at the injection site.

Treatment related effects included a dose dependent trend of prolonged activated partial thromboplastin time (aPTT). Prothrombin time (PT) showed mild increases in the 5× group. During the study, coagulation parameters were measured at 6 and 24 hours post-administration of Zycosan on study days 0, 28, and 56. At 6-hours post administration of Zycosan on study day 28 and 56, aPTT values in the horses administered 15 mg/kg Zycosan (5×) were 190 seconds (laboratory reference range 28-44 seconds). By 24 hours post-injection, aPTT values in the 5× horses remained high, with values ranging from 57.1 to 76.9 seconds. Horses in the 3× group had at least a 2-fold prolongation compared with pre-dose values, with values ranging from 60.9 to 190 seconds at 6-hours post-administration on study day 28, and with values ranging from 67.3 to 165.4 seconds at 6 hours post-administration on study day 56. Minimally prolonged aPTT, as compared with pre-dose values, was noted in all horses in the 1× dose group at 6 hours post-dose timepoint on study days 0, 28, and 56 (average values ranged from 38.9 to 48.9 seconds). aPTT values for the 1× group returned to the normal reference range at 24 hours post-injection. No horses exhibited clinical signs of coagulopathy.

SDH and GGT values in the 5× dose group were higher when compared to the control group. Increased GGT values for the 5× horses stayed within the laboratory reference range. Three study horses (two 5× and one 3×) had SDH values increased above the reference range during the study.

STORAGE CONDITIONS:

Store at room temperature 68-77°F (20-25°C), with excursions to 59-86°F (15-30°C).

HOW SUPPLIED:

Zycosan (pentosan polysulfate sodium injection) is supplied in cartons with each carton containing four clear glass vials with 7.5 mL (1,875 mg) of pentosan polysulfate sodium per vial.

NDC 17033-461-75

Approved by FDA under NADA # 141-559

MANUFACTURED FOR:
Dechra Veterinary Products
7015 College Boulevard, Suite 525
Overland Park, KS 66211 USA

Zycosan is a registered trademark of Dechra Limited.

Rev. May 2023

PC5417B

PRINCIPAL DISPLAY PANEL - 7.5 mL Vial Carton

Zycosan™
(pentosan polysulfate sodium injection)
250 mg/mL
For intramuscular use in horses only

Caution: Federal law restricts this drug to use by or on the order of
a licensed veterinarian.

Net Contents:
4 single use vials containing 7.5 mL each

Approved by FDA under NADA # 141-559

Dechra